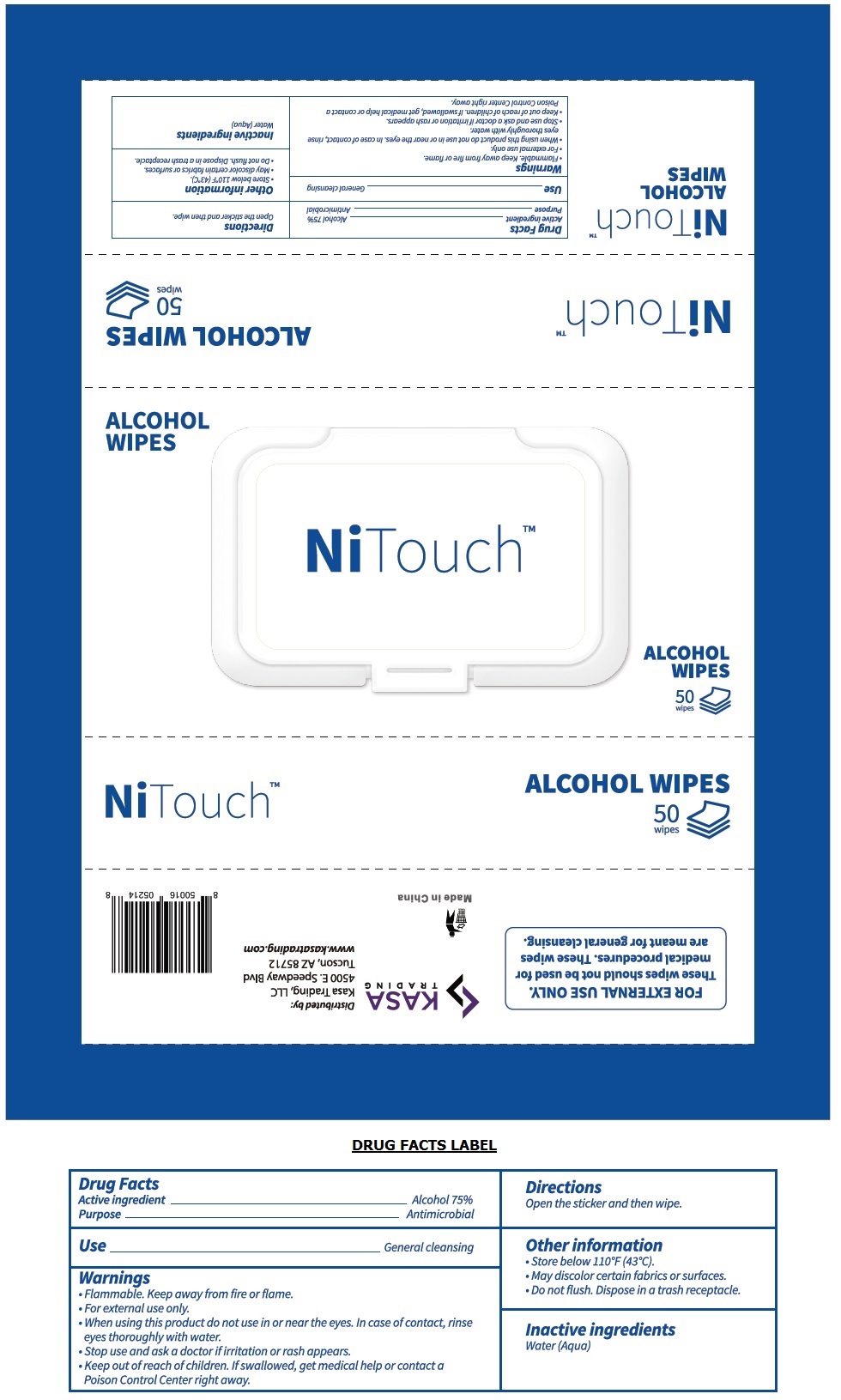 DRUG LABEL: NiTouch Alcohol Wipes
NDC: 80437-006 | Form: CLOTH
Manufacturer: Kasa Trading, Llc
Category: otc | Type: HUMAN OTC DRUG LABEL
Date: 20201028

ACTIVE INGREDIENTS: ALCOHOL 75 mL/100 mL
INACTIVE INGREDIENTS: WATER

NiTouchTM ALCOHOL WIPES

Active ingredient

Alcohol 75%

Purpose

Antimicrobial

Use

General cleansing

Warnings

• Flammable. Keep away from fire or flame.

• For external use only.

• When using this product do not use in or near the eyes. In case of contact, rinse eyes thoroughly with water.

• Stop use and ask a doctor if irritation or rash appears.

• Keep out of reach of children. If swallowed, get medical help or contact a Poison Control Center right away.

Directions

Open the sticker and then wipe.

Other information

• Store below 110°F (43°C).

• May discolor certain fabrics or surfaces.

• Do not flush. Dispose in a trash receptacle.

Inactive ingredients

Water (Aqua)

FOR EXTERNAL USE ONLY.

These wipes should not be used for medical procedures. These wipes are meant for general cleansing.

Distributed by:

Kasa Trading, LLC

4500 E. Speedway Blvd

Tucson, AZ 85712

www.kasatrading.com

Made in China